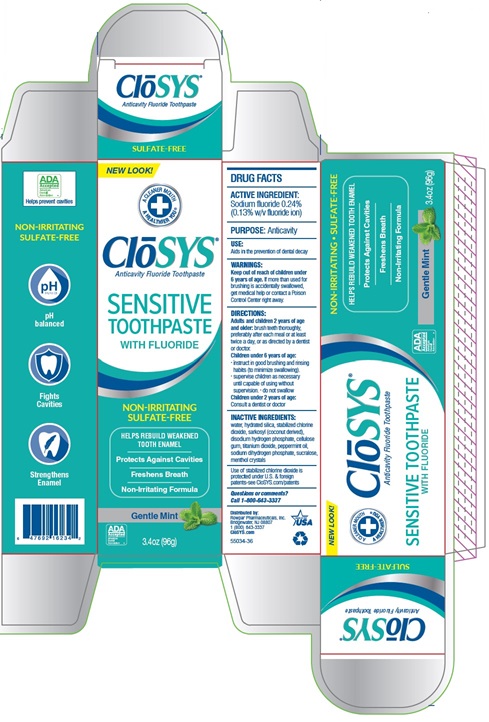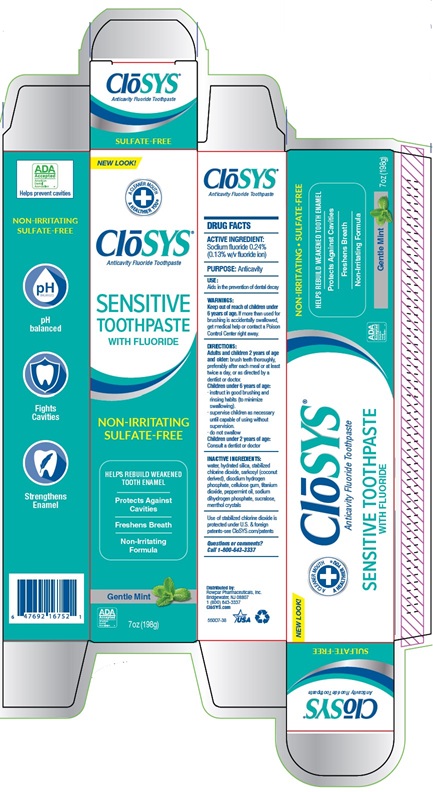 DRUG LABEL: CloSYS
NDC: 58578-0749 | Form: PASTE, DENTIFRICE
Manufacturer: Rowpar Pharmaceuticals, Inc.
Category: otc | Type: HUMAN OTC DRUG LABEL
Date: 20250516

ACTIVE INGREDIENTS: SODIUM FLUORIDE 1.1 mg/1 g
INACTIVE INGREDIENTS: SUCRALOSE; SODIUM PHOSPHATE, MONOBASIC, ANHYDROUS; SODIUM PHOSPHATE, DIBASIC, ANHYDROUS; CARBOXYMETHYLCELLULOSE; WATER; TITANIUM DIOXIDE; HYDRATED SILICA; CHLORINE DIOXIDE; PEPPERMINT OIL; MENTHOL; SODIUM LAUROYL SARCOSINATE

CloSYS Fluoride Toothpaste

ACTIVE INGREDIENT:

Sodium fluoride 0.24% (0.13% w/v fluoride ion)

PURPOSE:

Anticavity

USE:

Aids in the prevention of dental decay.

Keep out of reach of children under 6 years of age. If more than used for brushing is accidentally swallowed, get medical help or contact a Poison Control Center right away.

DIRECTIONS:

adults and children 2 years of age and older: brush teeth thoroughly, preferably after each meal or at least twice a day, or as directed by a dentist or doctor.

children under 6 years of age:

- instruct in good brushing and rinsing habits (to minimize swallowing).
- supervise children as necessary until capable of using without supervision.
- do not swallow

children under 2 years of age:

consult a dentist or doctor

INACTIVE INGREDIENTS:

water, hydrated silica, stabilized chlorine dioxide, sarkosyl (coconut derived), disodium hydrogen phosphate, cellulose gum, titanium dioxide, peppermint oil, sodium dihydrogen phosphate, sucralose, menthol crystals

Use of stabilized chlorine dioxide is protected under U.S. & foregin patents-see CloSYS.com/patents

Questions or comments?

Call 1-800-643-3337

Principal Display Panel

Closys®
Anticavity Fluoride Toothpaste
SULFATE-FREE
NEW LOOK!
A CLEANER MOUTH
A HEALTHIER YOU®
CLoSYS ®
Anticavity Fluoride Toothpaste
SENSITIVE
TOOTHPASTE
WITH FLUORIDE
NON-IRRITATING
SULFATE-FREE
HELPS REBUILD WEAKEND
TOOTH ENAMEL
Protects Against
Cavities
Freshens Breath
Non-Irritating
Formula
Gentle Mint
7oz (196g)
NON-IRRITATING
SULFATE-FREE
pH balanced
Fights
Cavities
Strengthens
Enamel
Closys®
Anticavity Fluoride Toothpaste
SENSITIVE TOOTHPASTE
WITH FLUORIDE
NON-IRRITATING SULFATE-FREE
HELPS REBUILD WEAKEND TOOTH ENAMEL
Protects Against Cavities
Freshens Breath
Non-Irritating Formula
Gentle Mint 7oz (196g)

Closys®
Anticavity Fluoride Toothpaste
SULFATE-FREE
NEW LOOK!
A CLEANER MOUTH
A HEALTHIER YOU®
CLoSYS ®
Anticavity Fluoride Toothpaste
SENSITIVE
TOOTHPASTE
WITH FLUORIDE
NON-IRRITATING
SULFATE-FREE
HELPS REBUILD WEAKEND
TOOTH ENAMEL
Protects Against
Cavities
Freshens Breath
Non-Irritating
Formula
Gentle Mint
3.4oz (96g)
NON-IRRITATING
SULFATE-FREE
pH balanced
Fights
Cavities
Strengthens
Enamel
Closys®
Anticavity Fluoride Toothpaste
SENSITIVE TOOTHPASTE
WITH FLUORIDE
NON-IRRITATING SULFATE-FREE
HELPS REBUILD WEAKEND TOOTH ENAMEL
Protects Against Cavities
Freshens Breath
Non-Irritating Formula
Gentle Mint 3.4oz (96g)